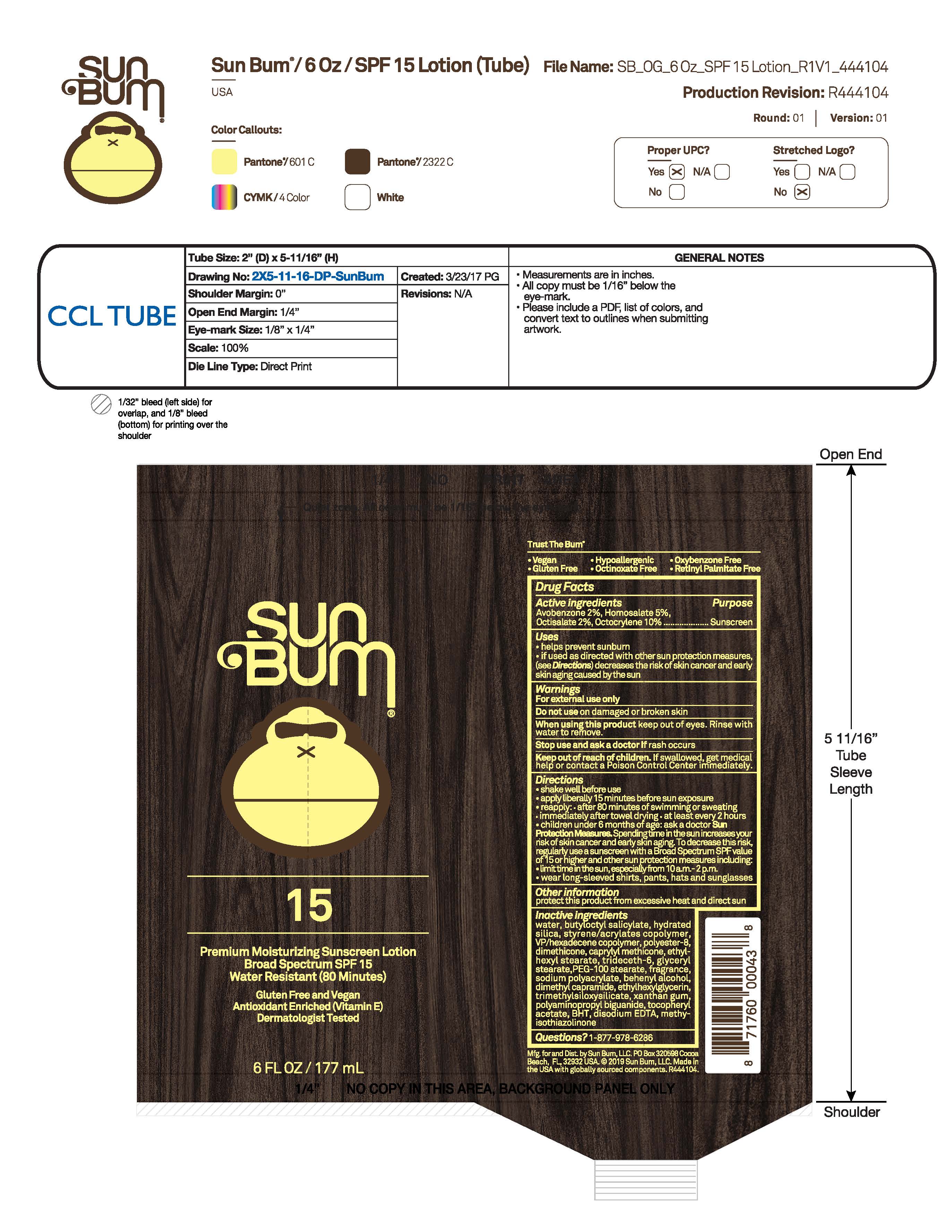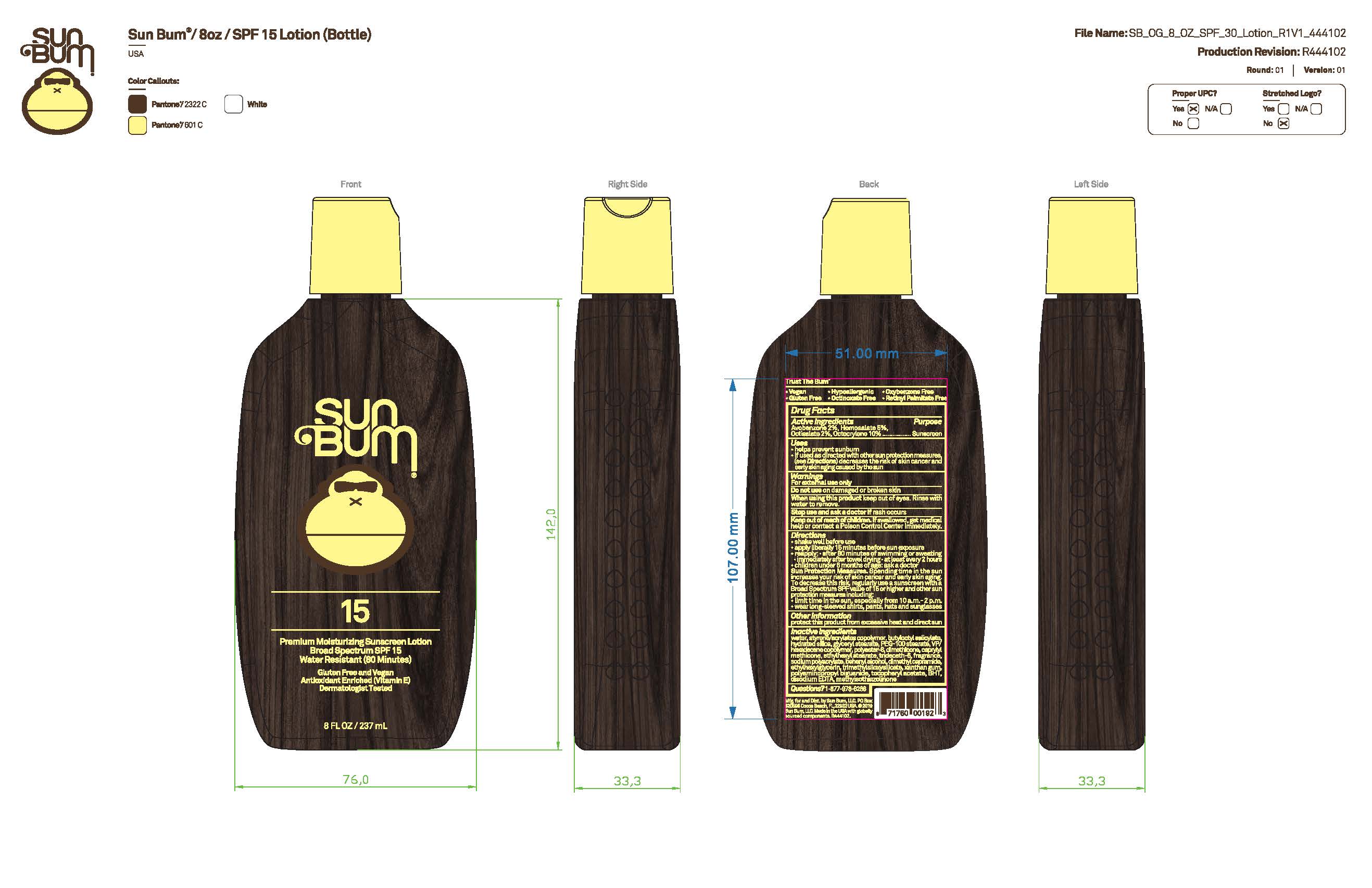 DRUG LABEL: Sun Bum 15 Premium Moisturizing Sunscreen 8 OZ
NDC: 69039-726 | Form: LOTION
Manufacturer: Sun Bum, LLC
Category: otc | Type: HUMAN OTC DRUG LABEL
Date: 20250814

ACTIVE INGREDIENTS: AVOBENZONE 20 mg/1 mL; OCTOCRYLENE 100 mg/1 mL; HOMOSALATE 50 mg/1 mL; OCTISALATE 20 mg/1 mL
INACTIVE INGREDIENTS: DIMETHICONE; TRIDECETH-6; BHT; EDETATE DISODIUM; POLYESTER-8 (1400 MW, CYANODIPHENYLPROPENOYL CAPPED); ETHYLHEXYL STEARATE; SODIUM POLYACRYLATE (8000 MW); XANTHAN GUM; POLYAMINOPROPYL BIGUANIDE; .ALPHA.-TOCOPHEROL ACETATE; WATER; BUTYLOCTYL SALICYLATE; PEG-100 STEARATE; DIMETHYL CAPRAMIDE; METHYLISOTHIAZOLINONE; VP/HEXADECENE COPOLYMER; ETHYLHEXYLGLYCERIN; TRIMETHYLSILOXYSILICATE (M/Q 0.66); GLYCERYL STEARATE; BEHENYL ALCOHOL; HYDRATED SILICA; LUVISET 360; CAPRYLYL METHICONE

Sun Bum 15 Premium Moisturizing Sunscreen - 6 OZ, 8 OZ

Active Ingredients

Avobenzone 2%, Homosalate 5%, Octisalate 2%, Octocrylene 10%

Purpose

Sunscreen

Uses

• helps prevent sunburn • if used as directed with other sun protection measures, (see Directions) decreases the risk of skin cancer and early skin aging caused by the sun

Warnings

For external use only

Do not use on damaged or broken skin

When using this product keep out of eyes. Rinse with water to remove.

Stop use and ask a doctor if rash occurs

Keep out of reach of children. If swallowed, get medical help or contact a Poison Control Center immediately.

Warnings

Keep Out Of Reach Of Children

Directions

• shake well before use

• apply liberally 15 minutes before sun exposure

• reapply: • after 80 minutes of swimming or sweating • immediately after towel drying • at least every 2 hours

• children under 6 months of age: ask a doctor

• Sun Protection Measures. Spending time in the sun increases your risk of skin cancer and early skin aging. To decrease this risk, regularly use a sunscreen with a Broad Spectrum SPF value of 15 or higher and other sun protection measures including:

• limit time in the sun, especially from 10 a.m.- 2 p.m.

• wear long-sleeved shirts, pants, hats and sunglasses

Directions

• shake well before use

• apply liberally 15 minutes before sun exposure

Other Information

protect this product from excessive heat and direct sun

Inactive Ingredients

water, butyloctyl salicylate, hydrated silica, styrene/acrylates copolymer, dimethicone, VP/hexadecene copolymer, polyester-8, caprylyl methicone, ethylhexyl stearate, trideceth-6, glyceryl stearate, PEG-100 stearate, fragrance, sodium polyacrylate, behenyl alcohol, dimethyl capramide, ethylhexylglycerin, trimethylsiloxysilicate, xanthan gum, polyaminopropyl biguanide, tocopheryl acetate, BHT, disodium EDTA, methyisothiazolinone

Questions?

1-877-978-6286